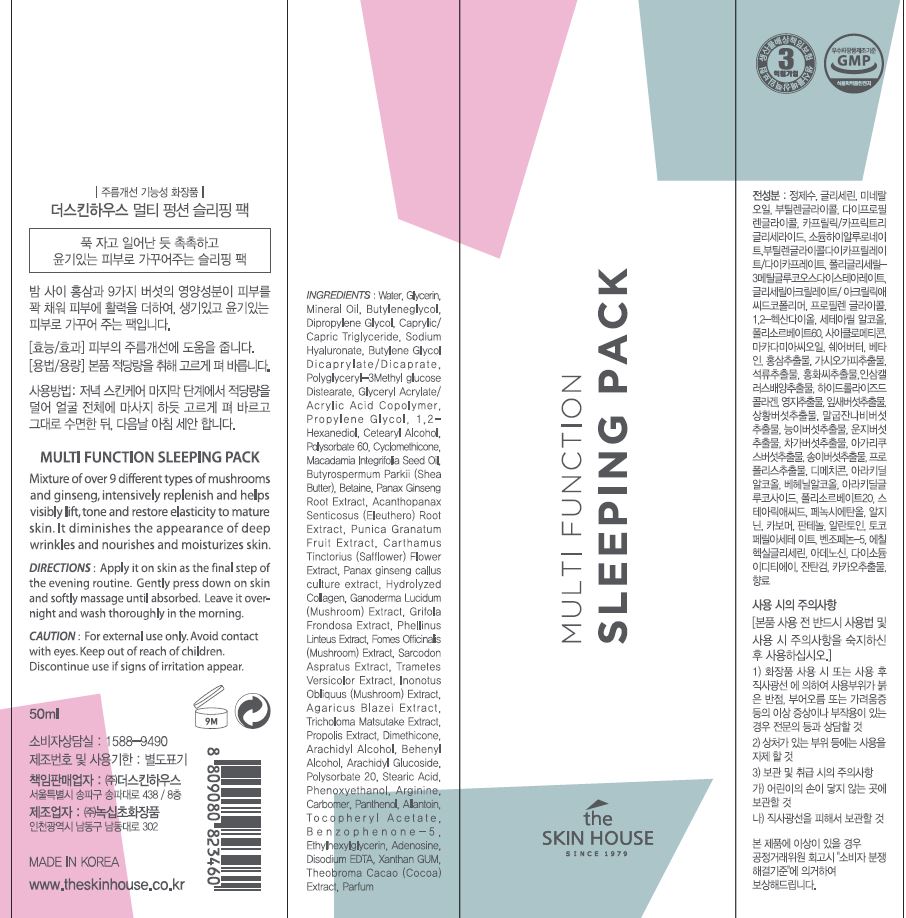 DRUG LABEL: MULTI FUNCTION SLEEPING PACK
NDC: 73590-0054 | Form: LIQUID
Manufacturer: NOKSIBCHO cosmetic Co., Ltd.
Category: otc | Type: HUMAN OTC DRUG LABEL
Date: 20200907

ACTIVE INGREDIENTS: ADENOSINE 0.04 g/100 mL
INACTIVE INGREDIENTS: WATER

Drug Facts

ACTIVE INGREDIENT

adenosine

INACTIVE INGREDIENT

Water
Glycerin
Mineral Oil
Butylene glycol
Dipropylene Glycol
Caprylic/Capric Triglyceride
Sodium Hyaluronate
Butylene Glycol Dicaprylate/Dicaprate
Polyglyceryl-3 Methylglucose Distearate
Glycerin
Glyceryl Acrylate/Acrylic Acid Copolymer
Propylene Glycol
1,2-Hexanediol
Cetearyl Alcohol
Polysorbate 60
Cyclomethicone
Macadamia Integrifolia Seed Oil
Butyrospermum Parkii (Shea Butter)
Betaine
Panax Ginseng Root Extract
Acanthopanax Senticosus (Eleuthero) Root Extract
Punica Granatum Fruit Extract
Carthamus Tinctorius (Safflower) Flower Extract
Panax ginseng callus culture extract
Hydrolyzed Collagen
Ganoderma Lucidum (Mushroom) Extract
Grifola Frondosa Extract
Phellinus Linteus Extract
Fomes Officinalis (Mushroom) Extract
Sarcodon Aspratus Extract
Trametes Versicolor Extract
Inonotus Obliquus (Mushroom) Extract
Agaricus Blazei Extract
Tricholoma Matsutake Extract
Propolis Extract
Cetearyl Alcohol
Dimethicone
Arachidyl Alcohol
Behenyl Alcohol
Arachidyl Glucoside
Polysorbate 20
Stearic Acid
Phenoxyethanol
Arginine
Carbomer
Panthenol
Allantoin
Tocopheryl Acetate
Benzophenone-5
Ethylhexylglycerin
Disodium EDTA
Xanthan GUM
Theobroma Cacao (Cocoa) Extract
Parfum

PURPOSE

wrinkle care

keep out of reach of the children

INDICATIONS AND USAGE

apply proper amount to the skin

WARNINGS

For external use only
When using this product

■ if the following symptoms occurs after use, stop use and consult with a skin specialist

red specks, swelling, itching

■ don’t use on the part where there is injury, eczema, or dermatitis

Keep out of reach of children

■ if swallowed, get medical help or contact a person control center immediately